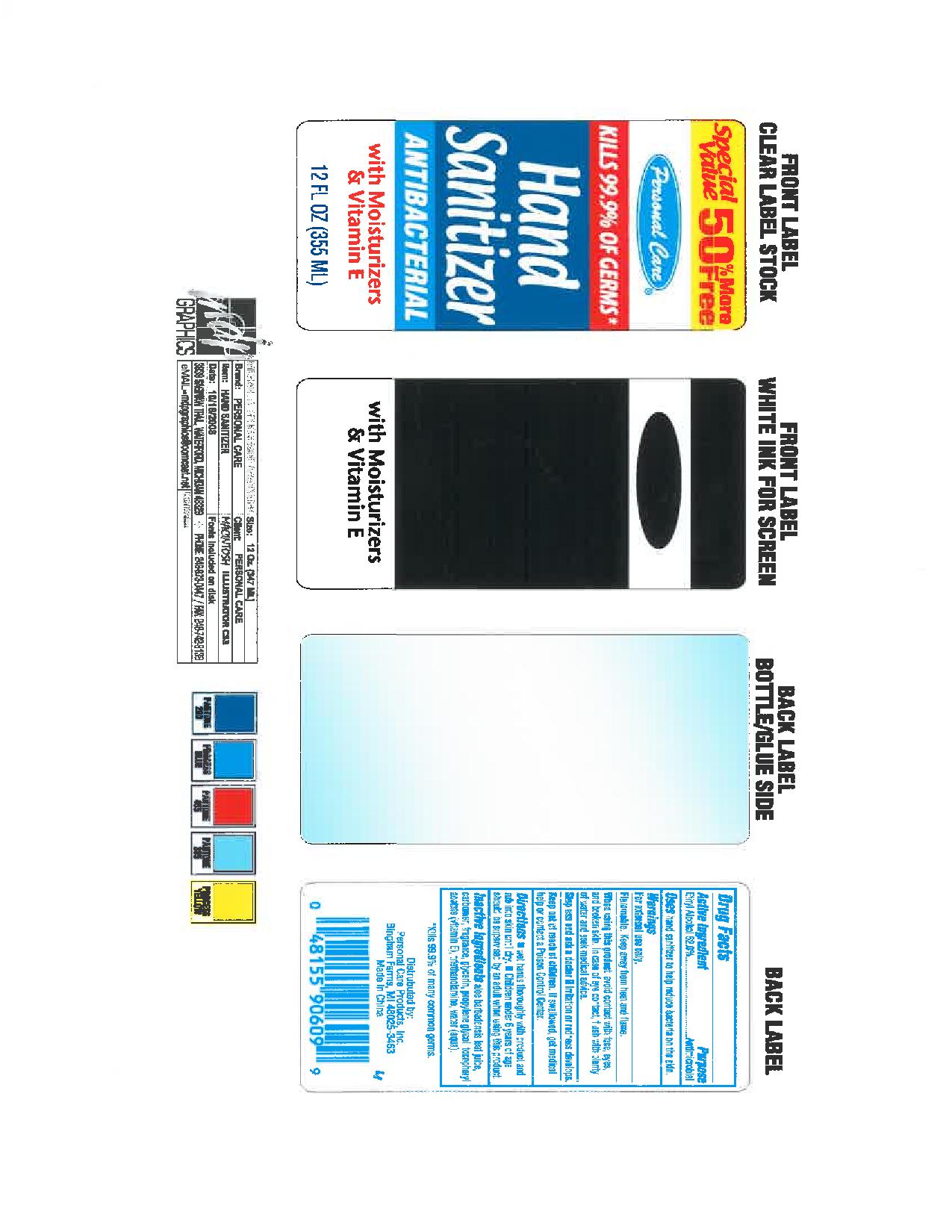 DRUG LABEL: Hand Sanitizer
NDC: 29500-910 | Form: GEL
Manufacturer: Personal Care Products
Category: otc | Type: HUMAN OTC DRUG LABEL
Date: 20110815

ACTIVE INGREDIENTS: alcohol 184.6 mL/355 mL
INACTIVE INGREDIENTS: ALOE VERA LEAF; GLYCERIN; PROPYLENE GLYCOL; ALPHA-TOCOPHEROL ACETATE; TROLAMINE; WATER

Hand Sanitizer

Active Ingredient Ethyl Alcohol 52.0%

Purpose Antimicrobial

Keep out of reach of children. If swallowed, get medical help or contact a Poison Control Center.

INDICATIONS AND USAGE

Uses hand sanitizer to help reduce bacteria on the skin.

Warnings

For external use only.

Flammable. Keep away from heat and flame.

When using this product avoid contact with face, eyes, and broken skin. In case of eye contact, flush with plenty of water and seek medical advice.

Stop use and ask a doctor if irritation or redness develops.

Directions

Wet hands thoroughly with product and rub into skin until dry

Children under 6 years of age should be supervised by an adult when using this product.

Inactive Ingredients

Aloe barbadensis leaf juice, carboner, fragrance, glycerin, propylene glycol, tocephenyl acetate (Vitamin E), triethanomolamine, water (aqua)

PACKAGE LABEL

Special value 50% more free

Personal Care

Kills 99.9% of germs*

Hand Sanitizer

Antibacterial with Moisturizers and Vitamin E

12 fl oz. (355 ml)